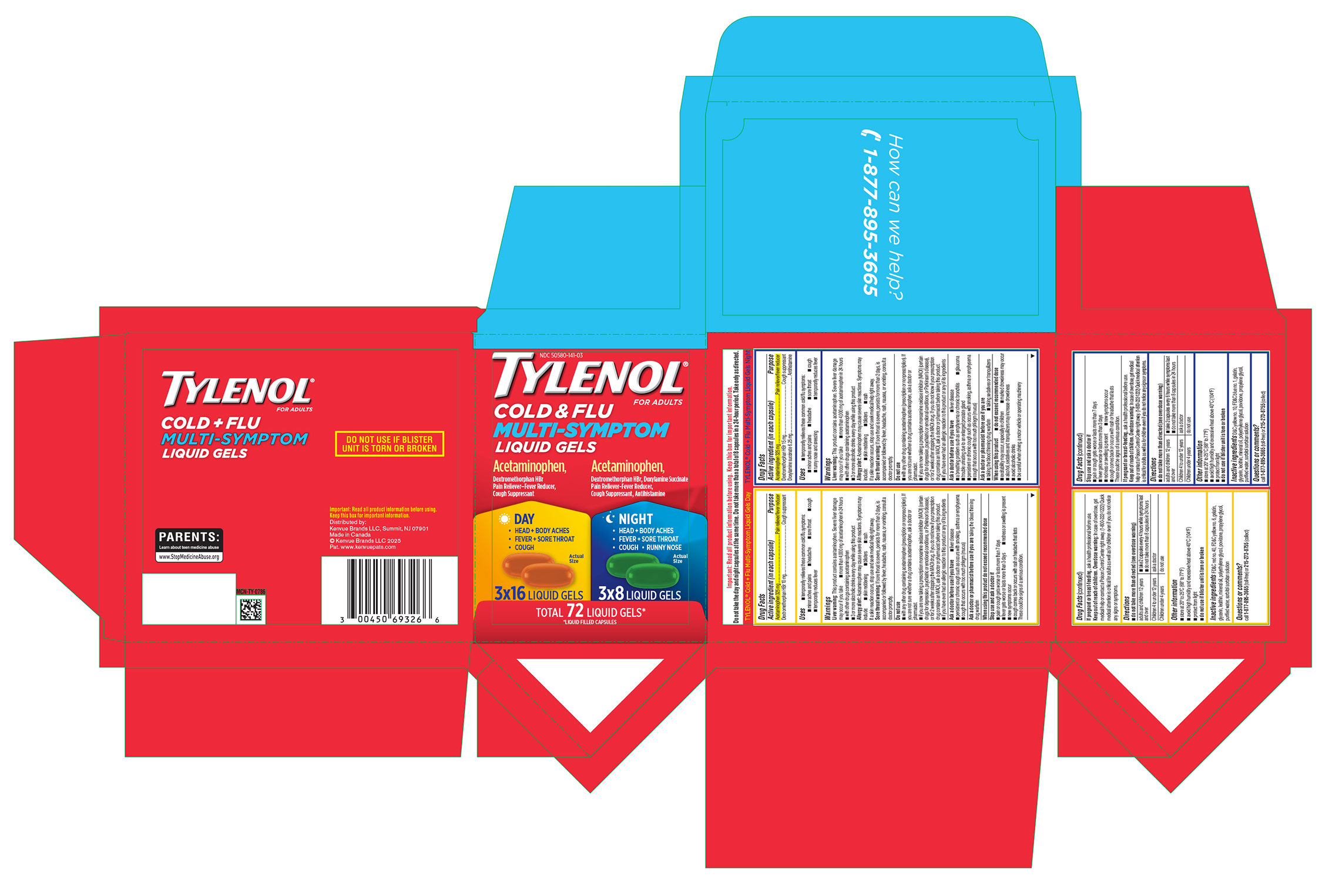 DRUG LABEL: TYLENOL Cold Plus Flu Multi-Symptom Liquid Gels Day Plus Night
NDC: 50580-141 | Form: KIT | Route: ORAL
Manufacturer: Kenvue Brands LLC
Category: otc | Type: HUMAN OTC DRUG LABEL
Date: 20260206

ACTIVE INGREDIENTS: DEXTROMETHORPHAN HYDROBROMIDE 10 mg/1 1; ACETAMINOPHEN 325 mg/1 1; DOXYLAMINE SUCCINATE 6.25 mg/1 1; ACETAMINOPHEN 325 mg/1 1; DEXTROMETHORPHAN HYDROBROMIDE 15 mg/1 1
INACTIVE INGREDIENTS: FD&C YELLOW NO. 6; GELATIN; GLYCERIN; MINERAL OIL; POLYETHYLENE GLYCOL, UNSPECIFIED; PROPYLENE GLYCOL; POVIDONE; WATER; FD&C RED NO. 40; GELATIN; GLYCERIN; WATER; POLYETHYLENE GLYCOL, UNSPECIFIED; MINERAL OIL; D&C YELLOW NO. 10; PROPYLENE GLYCOL; POVIDONE; FD&C BLUE NO. 1

TYLENOL® Cold + Flu Multi-Symptom Liquid Gels Day + Night

Drug Facts

TYLENOL® Cold + Flu Multi-Symptom Liquid Gels Day

Active ingredient (in each capsule)

Acetaminophen 325 mg
Dextromethorphan HBr 10 mg

PURPOSE

Pain reliever/fever reducer
Cough suppressant

Uses

■ temporarily relieves these common cold/flu symptoms:
■ minor aches and pains
■ headache
■ sore throat
■ cough
■ temporarily reduces fever

Warnings

Liver warning

This product contains acetaminophen. Severe liver damage may occur if you take
■ more than 4,000 mg of acetaminophen in 24 hours
■ with other drugs containing acetaminophen
■ 3 or more alcoholic drinks every day while using this product

Allergy alert

Acetaminophen may cause severe skin reactions. Symptoms may include:
■ skin reddening
■ blisters
■ rash
If a skin reaction occurs, stop use and seek medical help right away.

Sore throat warning

If sore throat is severe, persists for more than 2 days, is accompanied or followed by fever, headache, rash, nausea, or vomiting, consult a doctor promptly.

Do not use

■ with any other drug containing acetaminophen (prescription or nonprescription). If you are not sure whether a drug contains acetaminophen, ask a doctor or pharmacist.
■ if you are now taking a prescription monoamine oxidase inhibitor (MAOI) (certain drugs for depression, psychiatric or emotional conditions, or Parkinson’s disease), or for 2 weeks after stopping the MAOI drug. If you do not know if your prescription drug contains an MAOI, ask a doctor or pharmacist before taking this product.
■ if you have ever had an allergic reaction to this product or any of its ingredients

Ask a doctor before use if you have

■ liver disease
■ persistent or chronic cough such as occurs with smoking, asthma or emphysema
■ cough that occurs with too much phlegm (mucus)

Ask a doctor or pharmacist before use if you are taking the blood thinning drug warfarin

When using this product do not exceed recommended dose

Stop use and ask a doctor if
■ pain or cough gets worse or lasts more than 7 days
■ fever gets worse or lasts more than 3 days
■ redness or swelling is present
■ new symptoms occur
■ cough comes back or occurs with rash or headache that lasts
These could be signs of a serious condition.

PREGNANCY OR BREAST FEEDING

If pregnant or breast-feeding, ask a health professional before use.

Keep out of reach of children.

Overdose warning

In case of overdose, get medical help or contact a Poison Control Center right away. (1-800-222-1222) Quick medical attention is critical for adults as well as for children even if you do not notice any signs or symptoms.

Directions

■ do not take more than directed (see overdose warning)

adults and children 12 years and over | ■ take 2 capsules every 4 hours while symptoms last ■ do not take more than 8 capsules in 24 hours
Children 4 to under 12 years | ask a doctor
Children under 4 years | do not use

Other information

■ store at 20° to 25°C (68° to 77°F)
■ avoid high humidity and excessive heat above 40°C (104°F)
■ protect from light
■ do not use if blister unit is torn or broken

Inactive ingredients

FD&C red no. 40, FD&C yellow no. 6, gelatin, glycerin,lecithin, mineral oil, polyethylene glycol, povidone, propylene glycol, purified water,sorbitol sorbitan solution

Questions or comments?

call 1-877-895-3665 (toll-free) or 215-273-8755 (collect)

Drug Facts

TYLENOL® Cold + Flu Multi-Symptom Liquid Gels Night

Active ingredient (in each capsule)

Acetaminophen 325 mg
Dextromethorphan HBr 15 mg
Doxylamine succinate 6.25 mg

PURPOSE

Pain reliever/fever reducer

Cough suppressant

Antihistamine

Uses

■ temporarily relieves these common cold/flu symptoms:
■ minor aches and pains
■ headache
■ sore throat
■ cough
■ runny nose and sneezing
■ temporarily reduces fever

Warnings

Liver warning

This product contains acetaminophen. Severe liver damage may occur if you take
■ more than 4,000 mg of acetaminophen in 24 hours
■ with other drugs containing acetaminophen
■ 3 or more alcoholic drinks every day while using this product

Allergy alert:

Acetaminophen may cause severe skin reactions. Symptoms may include:
■ skin reddening
■ blisters
■ rash
If a skin reaction occurs, stop use and seek medical help right away.

Sore throat warning

If sore throat is severe, persists for more than 2 days, is accompanied or followed by fever, headache, rash, nausea, or vomiting, consult a doctor promptly.

Do not use

■ with any other drug containing acetaminophen (prescription or nonprescription). If you are not sure whether a drug contains acetaminophen, ask a doctor or pharmacist.
■ if you are now taking a prescription monoamine oxidase inhibitor (MAOI) (certain drugs for depression, psychiatric or emotional conditions, or Parkinson’s disease), or for 2 weeks after stopping the MAOI drug. If you do not know if your prescription drug contains an MAOI, ask a doctor or pharmacist before taking this product.
■ if you have ever had an allergic reaction to this product or any of its ingredients

Ask a doctor before use if you have

■ liver disease
■ a breathing problem such as emphysema or chronic bronchitis
■ glaucoma
■ trouble urinating due to an enlarged prostate gland
■ persistent or chronic cough such as occurs with smoking, asthma or emphysema
■ cough that occurs with too much phlegm (mucus)

Ask a doctor or pharmacist before use if you are
■ taking the blood thinning drug warfarin ■ taking sedatives or tranquilizers

WHEN USING

■do not exceed recommended dose
■ excitability may occur, especially in children
■ marked drowsiness may occur
■ alcohol, sedatives and tranquilizers may increase drowsiness
■ avoid alcoholic drinks
■ be careful when driving a motor vehicle or operating machinery

Stop use and ask a doctor if

■ pain or cough gets worse or lasts more than 7 days
■ fever gets worse or lasts more than 3 days
■ redness or swelling is present
■ new symptoms occur
■ cough comes back or occurs with rash or headache that lasts
These could be signs of a serious condition.

PREGNANCY OR BREAST FEEDING

If pregnant or breast-feeding, ask a health professional before use.

Keep out of reach of children.

Overdose warning

In case of overdose, get medical help or contact a Poison Control Center right away. (1-800-222-1222) Quick medical attention is critical for adults as well as for children even if you do not notice any signs or symptoms.

Directions

■ do not take more than directed (see overdose warning)

adults and children 12 years and over | ■ take 2 capsules every 6 hours while symptoms last ■ do not take more than 8 capsules in 24 hours
Children 4 to under 12 years | ask a doctor
Children under 4 years | do not use

Other information

■ store at 20° to 25°C (68° to 77°F)
■ avoid high humidity and excessive heat above 40°C (104°F)
■ protect from light
■ do not use if blister unit is torn or broken

Inactive ingredients

D&C yellow no. 10, FD&C blue no. 1, gelatin, glycerin,lecithin, mineral oil, polyethylene glycol, povidone, propylene glycol, purified water,sorbitol sorbitan solution

Questions or comments?

call 1-877-895-3665 (toll-free) or 215-273-8755 (collect)

PRINCIPAL DISPLAY PANEL

NDC 50580-141-03

TYLENOL®

FOR ADULTS

COLD & FLU
MULTI SYMPTOM
LIQUID GELS

Acetaminophen,
Dextromethorphan HBr
Pain Reliever–Fever Reducer,
Cough Suppressant

DAY
• HEAD + BODY ACHES
• FEVER + SORE THROAT
• COUGH

Actual Size

3X16 LIQUID GELS

Acetaminophen,

Dextromethorphan HBr, Doxylamine Succinate

Pain Reliever-Fever Reducer,
Cough Suppressant, Antihistamine

NIGHT
• HEAD + BODY ACHES
• FEVER + SORE THROAT
• COUGH • RUNNY NOSE

Actual Size

3X8 LIQUID GELS

TOTAL 72 LIQUID GELS*

*LIQUID FILLED CAPSULES